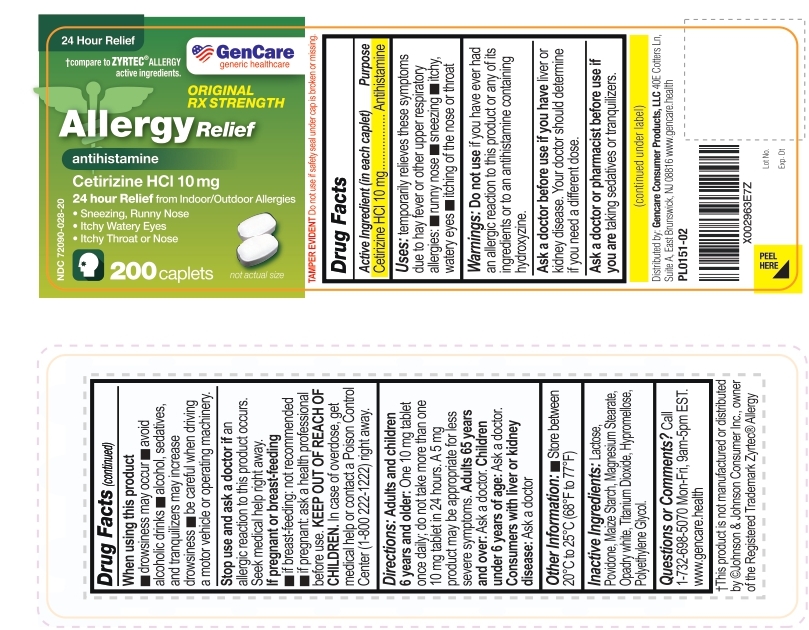 DRUG LABEL: Allergy Relief
NDC: 72090-028 | Form: TABLET
Manufacturer: Pioneer Life Sciences, LLC
Category: otc | Type: HUMAN OTC DRUG LABEL
Date: 20251223

ACTIVE INGREDIENTS: CETIRIZINE HYDROCHLORIDE 10 mg/1 1
INACTIVE INGREDIENTS: LACTOSE MONOHYDRATE; MAGNESIUM STEARATE; POLYETHYLENE GLYCOL, UNSPECIFIED; HYPROMELLOSE, UNSPECIFIED; TITANIUM DIOXIDE; STARCH, CORN; POVIDONE

Allergy relief

Active Ingredient (in each caplet)

Cetirizine HCl 10 mg

Purpose

Antihistamine

Uses:

- temporarily relieves these symptoms due to hay fever or other upper respiratory allergies:
- runny nose
- sneezing
- itchy, watery eyes
- itching of the nose or throat

Warnings:

Do not use

if you have ever had an allergic reaction to this product or any of its ingredients or to an antihistamine containing hydroxyzine.

Ask a doctor before use if you have liver or kidney disease. Your doctor should determine if you need a different dose.

Ask a doctor or pharmacist before use if you are taking sedatives or tranquilizers.

When using this product
• drowsiness may occur
• avoid alcoholic drinks
• alcohol, sedatives, and tranquilizers may increase drowsiness
• be careful when driving a motor vehicle or operating machinery

Stop use and ask a doctor if an allergic reaction to this product occurs. Seek medical help right away.

If pregnant or breast-feeding:
• if breast-feeding: not recommended
• if pregnant: ask a health professional before use

KEEP OUT OF REACH OF CHILDREN. In case of overdose, get medical help or contact a Poison Control Center (1-800 222-1222) right away.

Directions

Adults and children 6 years and older: One 10 mg tablet once daily; do not take more than one 10 mg tablet in 24 hours. A 5 mg product may be appropriate for less severe symptoms.

Adults 65 years and over: Ask a doctor.

Children under 6 years of age: Ask a doctor.

Consumers with liver or kidney disease: Ask a doctor

Other lnfonnation

- Store between 20°Cto 25°C(68°F to 77°F)

Inactive Ingredients

Lactose, Povidone, Maize Starch, Magnesium Stearate, Opadry White, Titanium Dioxide, Hypromellose, Polyethylene Glycol

Questions or Comments?

Call 1-732-698-5070 Mon-Fri, 9am-5pm EST.